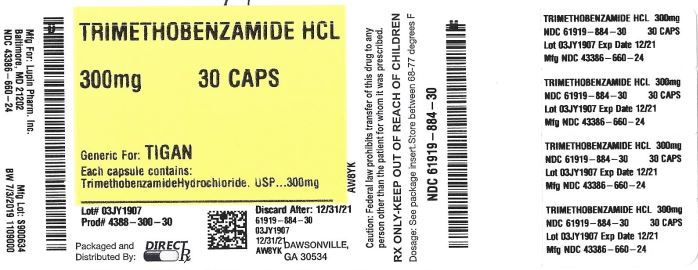 DRUG LABEL: Trimethobenzamide
NDC: 61919-884 | Form: CAPSULE
Manufacturer: Direct_Rx
Category: prescription | Type: HUMAN PRESCRIPTION DRUG LABEL
Date: 20230112

ACTIVE INGREDIENTS: TRIMETHOBENZAMIDE HYDROCHLORIDE 300 mg/1 1
INACTIVE INGREDIENTS: MAGNESIUM STEARATE; LACTOSE MONOHYDRATE; STARCH, CORN; FD&C RED NO. 40; LECITHIN, SOYBEAN; GELATIN; TITANIUM DIOXIDE; SHELLAC; D&C RED NO. 28; FD&C BLUE NO. 1; WATER; ETHYLENE GLYCOL MONOETHYL ETHER

Trimethobenzamide

DESCRIPTION

Chemically, trimethobenzamide hydrochloride is N-[ρ -[2-(dimethylamino)ethoxy]benzyl]-

3,4,5-trimethoxybenzamide monohydrochloride. It has a molecular weight of 424.92 and the following structural formula:

[b09aec67-figure-01]

Each capsule for oral use contains trimethobenzamide hydrochloride equivalent to 300 mg.

Inactive Ingredients: Lactose monohydrate, magnesium stearate and pregelatinized starch. The capsule shell contains the following ingredients: D&C Red #28, FD&C Blue #1, FD&C Red #40, gelatin and titanium dioxide.

White ink contains the following ingredients: 2-ethoxyethanol, industrial methylated spirit, lecithin, purified water, shellac glaze, simethicone emulsion and titanium dioxide.

CLINICAL PHARMACOLOGY

Mechanism of Action

The mechanism of action of trimethobenzamide hydrochloride as determined in animals is obscure, but may involve the chemoreceptor trigger zone (CTZ), an area in the medulla oblongata through which emetic impulses are conveyed to the vomiting center; direct impulses to the vomiting center apparently are not similarly inhibited. In dogs pretreated with trimethobenzamide hydrochloride, the emetic response to apomorphine is inhibited, while little or no protection is afforded against emesis induced by intragastric copper sulfate.

Pharmacokinetics

The pharmacokinetics of trimethobenzamide have been studied in healthy adult subjects. Following administration of 200 mg (100 mg/mL) trimethobenzamide I.M. injection, the time to reach maximum plasma concentration (Tmax) was about half an hour, about 15 minutes longer for trimethobenzamide 300 mg oral capsule than an I.M. injection. A single dose of trimethobenzamide 300 mg oral capsule provided a plasma concentration profile of trimethobenzamide similar to trimethobenzamide 200 mg I.M. The relative bioavailability of the capsule formulation compared to the solution is 100%. The mean elimination half-life of trimethobenzamide is 7 to 9 hours. Between 30 – 50 % of a single dose in humans is excreted unchanged in the urine within 48 – 72 hours. The major pathway of trimethobenzamide metabolism is through oxidation resulting in the formation of trimethobenzamide N-oxide metabolite. The pharmacologic activity of this major metabolite has not been evaluated.

Special Populations

Age

The clearance of trimethobenzamide is not known in patients with renal impairment. However, it may be advisable to consider reduction in the dosing of trimethobenzamide in elderly patients with renal impairment considering that a substantial amount of excretion and elimination of trimethobenzamide occurs via the kidney and that elderly patients may have various degrees of renal impairment. (See PRECAUTIONS: General and DOSAGE AND ADMINISTRATION).

Gender

Systemic exposure to trimethobenzamide was similar between men (N=40) and women (N=28).

Race

Pharmacokinetics appeared to be similar for Caucasians (N=53) and African Americans (N=12).

Renal Impairment

The clearance of trimethobenzamide is not known in patients with renal impairment. However, it may be advisable to consider reduction in the dosing of trimethobenzamide in patients with renal impairment considering that a substantial amount of excretion and elimination of trimethobenzamide occurs via the kidney. (See PRECAUTIONS: General and DOSAGE AND ADMNISTRATION).

INDICATIONS AND USAGE

Trimethobenzamide Hydrochloride Capsule, USP 300 mg is indicated for the treatment of postoperative nausea and vomiting and for nausea associated with gastroenteritis.

CONTRAINDICATIONS

Use of any dosage forms in patients with known hypersensitivity to trimethobenzamide is contraindicated.

WARNINGS

Caution should be exercised when administering trimethobenzamide hydrochloride capsules to children for the treatment of vomiting. Antiemetics are not recommended for treatment of uncomplicated vomiting in children and their use should be limited to prolonged vomiting of known etiology. There are two principal reasons for caution:

1. The extrapyramidal symptoms which can occur secondary to trimethobenzamide hydrochloride capsules may be confused with the central nervous system signs of an undiagnosed primary disease responsible for the vomiting, e.g., Reye's syndrome or other encephalopathy.

2. It has been suspected that drugs with hepatotoxic potential, such as trimethobenzamide hydrochloride capsules, may unfavorably alter the course of Reye's syndrome. Such drugs should therefore be avoided in children whose signs and symptoms (vomiting) could represent Reye's syndrome.

Trimethobenzamide hydrochloride capsules may produce drowsiness. Patients should not operate motor vehicles or other dangerous machinery until their individual responses have been determined.

Usage in Pregnancy: Trimethobenzamide hydrochloride was studied in reproduction experiments in rats and rabbits and no teratogenicity was suggested. The only effects observed were an increased percentage of embryonic resorptions or stillborn pups in rats administered 20 mg and 100 mg/kg and increased resorptions in rabbits receiving 100 mg/kg. In each study these adverse effects were attributed to one or two dams. The relevance to humans is not known. Since there is no adequate experience in pregnant or lactating women who have received this drug, safety in pregnancy or in nursing mothers has not been established.

Usage with Alcohol: Concomitant use of alcohol with trimethobenzamide hydrochloride capsules may result in an adverse drug interaction.

PRECAUTIONS

During the course of acute febrile illness, encephalitides, gastroenteritis, dehydration and electrolyte imbalance, especially in children and the elderly or debilitated, CNS reactions such as opisthotonos, convulsions, coma and extrapyramidal symptoms have been reported with and without use of trimethobenzamide hydrochloride capsules or other antiemetic agents. In such disorders caution should be exercised in administering trimethobenzamide hydrochloride capsules, particularly to patients who have recently received other CNS acting agents (phenothiazines, barbiturates, belladonna derivatives). Primary emphasis should be directed toward the restoration of body fluids and electrolyte balance, the relief of fever and relief of the causative disease process. Overhydration should be avoided since it may result in cerebral edema.

The antiemetic effects of trimethobenzamide hydrochloride capsules may render diagnosis more difficult in such conditions as appendicitis and obscure signs of toxicity due to overdosage of other drugs.

General

Adjustment of Dose in Renal Failure

A substantial route of elimination of unchanged trimethobenzamide is via the kidney. Dosage adjustment should be considered in patients with reduced renal function including some elderly patients. (See CLINICAL PHARMACOLOGY and DOSAGE AND ADMINISTRATION).

Geriatric Use

Clinical studies of trimethobenzamide hydrochloride did not include sufficient numbers of patients aged 65 and over to determine whether they respond differently from younger patients. Although there are studies reported in the literature that included elderly patients >65 years old with younger patients, it is not known if there are differences in efficacy or safety parameters for elderly and non-elderly patients treated with trimethobenzamide. In general, dose selection for an elderly patient should be cautious, usually starting at the low end of the dosing range, reflecting the greater frequency of decreased hepatic, renal, or cardiac function, and of concomitant disease or other drug therapy.

This drug is known to be substantially excreted by the kidney, and the risk of toxic reactions to this drug may be greater in patients with impaired renal function. Because elderly patients are more likely to have decreased renal function, care should be taken in dose selection, and it may be useful to monitor renal function. (See CLINCAL PHARMACOLOGY and DOSAGE AND ADMINISTRATION).

ADVERSE REACTIONS

There have been reports of hypersensitivity reactions and Parkinson-like symptoms. There have been instances of hypotension reported following parenteral administration to surgical patients. There have been reports of blood dyscrasias, blurring of vision, coma, convulsions, depression of mood, diarrhea, disorientation, dizziness, drowsiness, headache, jaundice, muscle cramps and opisthotonos. If these occur, the administration of the drug should be discontinued. Allergic-type skin reactions have been observed; therefore, the drug should be discontinued at the first sign of sensitization. While these symptoms will usually disappear spontaneously, symptomatic treatment may be indicated in some cases.

DOSAGE AND ADMINISTRATION

(See WARNINGS and PRECAUTIONS.)

Dosage should be adjusted according to the indication for therapy, severity of symptoms and the response of the patient.

Geriatric Patients

Dose adjustment such as reducing the total dose administered at each dosing or increasing the dosing interval should be considered in elderly patients with renal impairment (creatinine clearance ≤ 70 mL/min/1.73m2). Final dose adjustment should be based upon integration of clinical efficacy and safety considerations. (See CLINICAL PHARMACOLOGY and PRECAUTIONS).

Patients and Renal Impairment

In subjects with renal impairment (creatinine clearance ≤ 70 mL/min/1.73m2), dose adjustment such as reducing the total dose administered at each dosing or increasing the dosing interval should be considered. (See CLINICAL PHARMACOLOGY and PRECAUTIONS).

Usual Adult Dosage: One 300 mg capsule 3 or 4 times daily.

STORAGE

Store at 20° to 25°C (68° to 77°F) [See USP Controlled Room Temperature].

HOW SUPPLIED

Trimethobenzamide Hydrochloride Capsules, USP 300 mg are filled gelatin capsules size 1 lavender opaque cap/lavender opaque body with a white imprint "Novel 660" on cap and "300 mg" on body.

Available in bottles of 30's

Bottles of 100 capsules

Bottles of 500 capsules:

Manufactured by:

Novel Laboratories, Inc.

Somerset, NJ 08873

Distributed by

Lupin Pharmaceuticals, Inc

Baltimore, MD 21202

PI6600000204

Rev. 05/2016